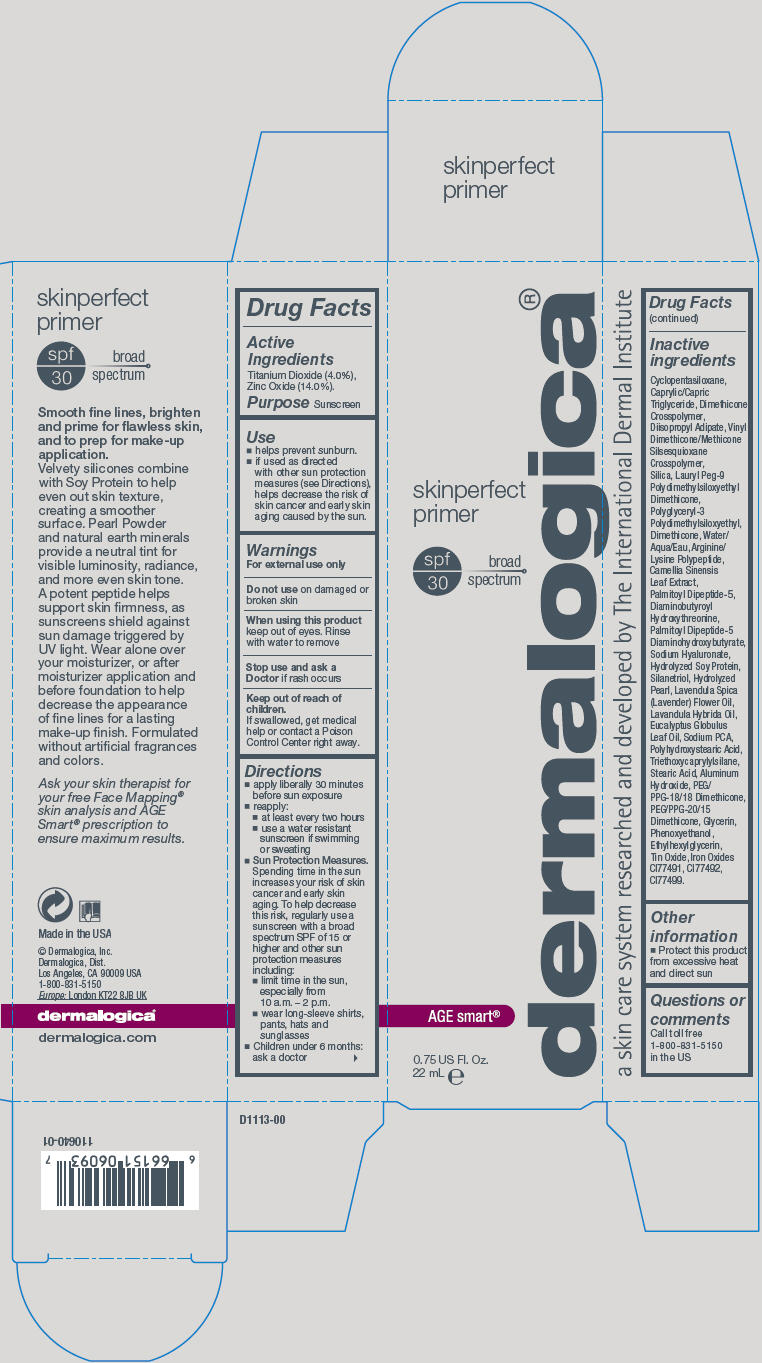 DRUG LABEL: SkinPerfect Primer 
NDC: 68479-130 | Form: LOTION
Manufacturer: Dermalogica, Inc.
Category: otc | Type: HUMAN OTC DRUG LABEL
Date: 20171205

ACTIVE INGREDIENTS: Titanium Dioxide 40 mg/1 mL; Zinc Oxide 140 mg/1 mL
INACTIVE INGREDIENTS: Cyclomethicone 5; Diisopropyl Adipate; Medium-Chain Triglycerides; Lauryl PEG-9 Polydimethylsiloxyethyl Dimethicone; Green Tea Leaf; Hyaluronate Sodium; Calcium Carbonate; Silanetriol; Lavender Oil; Lavandin Oil; Eucalyptus Oil; Sodium Pyrrolidone Carboxylate; Polyhydroxystearic Acid (2300 MW); Triethoxycaprylylsilane; Aluminum Hydroxide; Stearic Acid; PEG/PPG-18/18 Dimethicone; PEG/PPG-20/15 Dimethicone; Glycerin; Phenoxyethanol; Ethylhexylglycerin; Stannic Oxide; Ferric Oxide Red; Ferric Oxide Yellow; Ferrosoferric Oxide

SkinPerfect Primer
SPF 30

Drug Facts

Active Ingredients

Titanium Dioxide (4.0%), Zinc Oxide (14.0%).

Purpose

Sunscreen

Use

- helps prevent sunburn.
- if used as directed with other sun protection measures (see Directions), helps decrease the risk of skin cancer and early skin aging caused by the sun.

Warnings

For external use only

Do not use on damaged or broken skin

When using this product keep out of eyes. Rinse with water to remove

Stop use and ask a Doctor if rash occurs

Keep out of reach of children.

If swallowed, get medical help or contact a Poison Control Center right away.

Directions

- apply liberally 30 minutes before sun exposure
- reapply:
  - at least every two hours
  - use a water resistant sunscreen if swimming or sweating
- Sun Protection Measures. Spending time in the sun increases your risk of skin cancer and early skin aging. To help decrease this risk, regularly use a sunscreen with a broad spectrum SPF of 15 or higher and other sun protection measures including:
  - limit time in the sun, especially from 10 a.m. – 2 p.m.
  - wear long-sleeve shirts, pants, hats and sunglasses
- Children under 6 months: ask a doctor

Inactive ingredients

Cyclopentasiloxane, Caprylic/Capric Triglyceride, Dimethicone Crosspolymer, Diisopropyl Adipate, Vinyl Dimethicone/Methicone Silsesquioxane Crosspolymer, Silica, Lauryl Peg-9 Polydimethylsiloxyethyl Dimethicone, Polyglyceryl-3 Polydimethylsiloxyethyl, Dimethicone, Water/Aqua/Eau, Arginine/Lysine Polypeptide, Camellia Sinensis Leaf Extract, Palmitoyl Dipeptide-5, Diaminobutyroyl Hydroxythreonine, Palmitoyl Dipeptide-5 Diaminohydroxybutyrate, Sodium Hyaluronate, Hydrolyzed Soy Protein, Silanetriol, Hydrolyzed Pearl, Lavendula Spica (Lavender) Flower Oil, Lavandula Hybrida Oil, Eucalyptus Globulus Leaf Oil, Sodium PCA, Polyhydroxystearic Acid, Triethoxycaprylylsilane, Stearic Acid, Aluminum Hydroxide, PEG/PPG-18/18 Dimethicone, PEG/PPG-20/15 Dimethicone, Glycerin, Phenoxyethanol, Ethylhexylglycerin, Tin Oxide, Iron Oxides CI77491, CI77492, CI77499.

Other information

- Protect this product from excessive heat and direct sun

Questions or comments

Call toll free 1-800-831-5150 in the US

PRINCIPAL DISPLAY PANEL - 22 mL Tube Carton

skinperfect
primer

spf
30

broad
spectrum

AGE smart®

0.75 US Fl. Oz.
22 mL e

dermalogica®